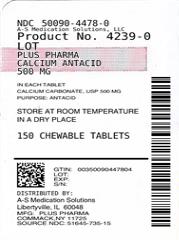 DRUG LABEL: Plus Pharma
NDC: 50090-4478 | Form: TABLET, CHEWABLE
Manufacturer: A-S Medication Solutions
Category: otc | Type: HUMAN OTC DRUG LABEL
Date: 20210415

ACTIVE INGREDIENTS: CALCIUM CARBONATE 500 mg/1 1
INACTIVE INGREDIENTS: ACACIA; SILICON DIOXIDE; D&C RED NO. 27; FD&C BLUE NO. 1; MAGNESIUM STEARATE; MALTODEXTRIN; MICROCRYSTALLINE CELLULOSE; STARCH, CORN; SUCROSE

Calcium Antacid

Active ingredient (in each tablet)

Calcium Carbonate, USP 500 mg

Purpose

Antacid

Uses

for the relief of

- heartburn
- sour stomach
- acid indigestion
- upset stomach associated with these symptoms

Warnings

Do not take more than 15 tablets in a 24-hour period, or use the maximum dosage of this product for more than 2 weeks, except under the advice and supervision of a doctor.

Ask a doctor or pharmacist before use if you are

- presently taking a prescription drug. Antacids may interact with certain prescription drugs.

If pregnant or breast-feeding,

ask a doctor before use.

Directions

Adults and children 12 years and older
Chew 2 tablets every 2 or 3 hours as symptoms occur or as directed by a doctor

Children under 12 years
Do not give to children under 12 years unless directed by a doctor

Other information

- Each tablet contains: Elemental Calcium 195 mg
- Each tablet contains: Sugar 1g
- Do not exceed recommended dosage
- Store at room temperature in a dry place
- Do not use if clear neck seal is broken or missing

Inactive ingredients

Acacia, Artificial Cherry Flavor, Artificial Red Berry Flavor, Colloidal Silica, D and C Red #27 Lake, FD and C Blue #1 Lake, Magnesium Stearate, Maltodextrin, Microcrystalline Cellulose, Natural and Artificial Spearmint Flavor, Strach, Sucrose

Questions?

If you have any questions or comments, or to report an adverse event, please contact (800) 795-9775.

HOW SUPPLIED

Product: 50090-4478

NDC: 50090-4478-0 150 TABLET, CHEWABLE in a BOTTLE, PLASTIC